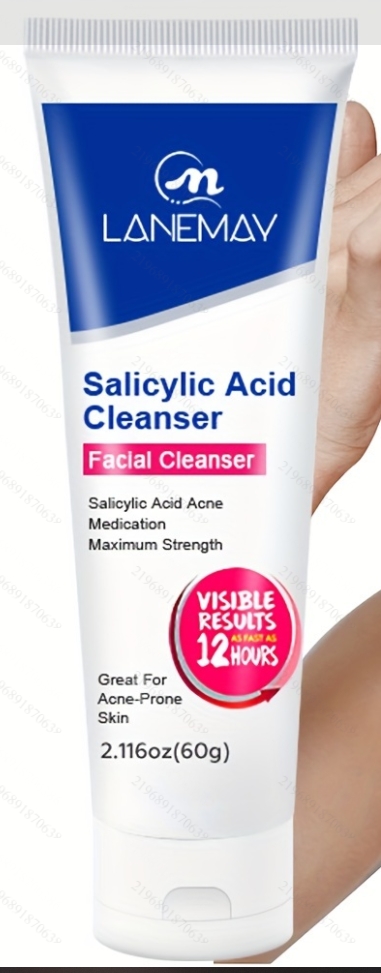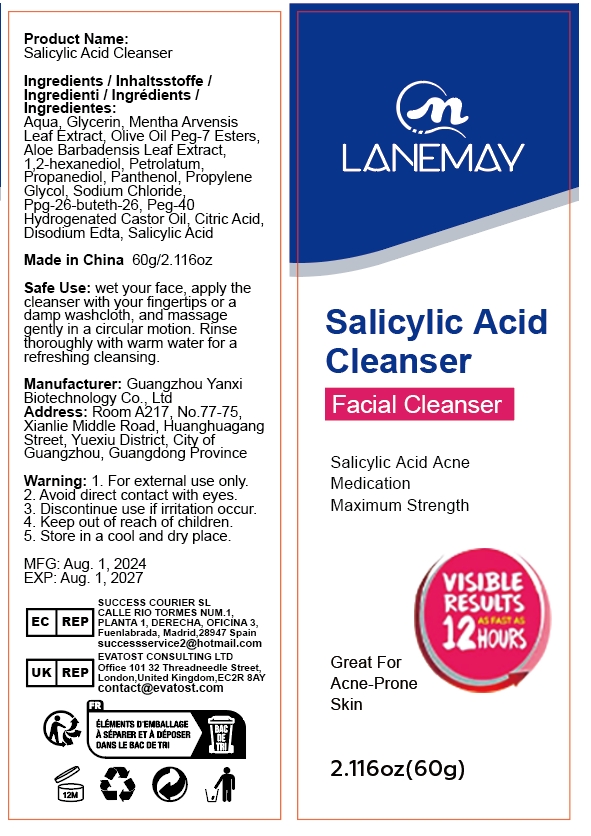 DRUG LABEL: Salicylic Acid Cleanser
NDC: 84025-263 | Form: CREAM
Manufacturer: Guangzhou Yanxi Biotechnology Co., Ltd
Category: otc | Type: HUMAN OTC DRUG LABEL
Date: 20241115

ACTIVE INGREDIENTS: PETROLATUM 2 mg/60 g; GLYCERIN 3 mg/60 g
INACTIVE INGREDIENTS: WATER

DOSAGE AND ADMINISTRATION

wet your face, apply the cleanser with your fingertips or a damp washcloth,and massage gently in a circular motion.Rinse thoroughly with warm water for a refreshing cleansing.

WARNINGS

Keep out of children

INACTIVE INGREDIENT

Aqua

Keep out of children

INDICATIONS AND USAGE

For daily skin clean

PURPOSE

Facial Cleanser